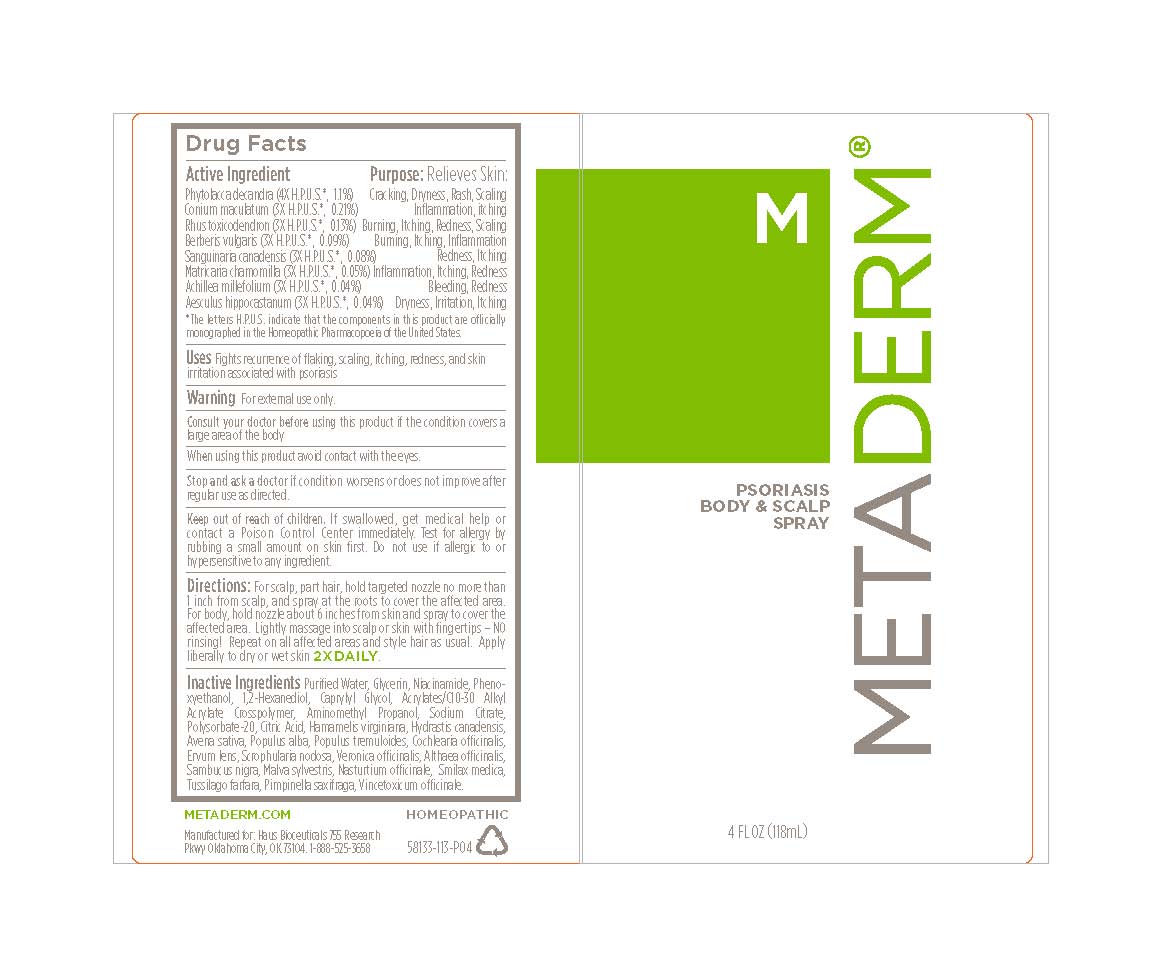 DRUG LABEL: Metaderm Psoriasis Body and Scalp
NDC: 58133-391 | Form: SPRAY
Manufacturer: Cosmetic Specialty Labs, Inc.
Category: homeopathic | Type: HUMAN OTC DRUG LABEL
Date: 20180816

ACTIVE INGREDIENTS: MATRICARIA CHAMOMILLA FLOWERING TOP OIL 5 [hp_M]/1 mL; SANGUINARIA CANADENSIS ROOT 8 [hp_M]/1 mL; ACHILLEA MILLEFOLIUM 4 [hp_M]/1 mL; BERBERIS VULGARIS FRUIT 9 [hp_M]/1 mL; CONIUM MACULATUM FRUIT 21 [hp_M]/1 mL; RHUS SPP. WHOLE 13 [hp_M]/1 mL; PHYTOLACCA OCTANDRA LEAF 110 [hp_M]/1 mL; AESCULUS HIPPOCASTANUM SEED OIL 4 [hp_M]/1 mL
INACTIVE INGREDIENTS: 1,2-HEXANEDIOL; POLYSORBATE 20; ANHYDROUS CITRIC ACID; VERONICA OFFICINALIS LEAF; ALTHAEA OFFICINALIS LEAF; SCROPHULARIA NODOSA; WATER; HAMAMELIS VIRGINIANA ROOT BARK/STEM BARK; PHENOXYETHANOL; CAPRYLYL GLYCOL; HYDRASTIS CANADENSIS WHOLE; TUSSILAGO FARFARA; LENS CULINARIS FRUIT; SAMBUCUS NIGRA FLOWER OIL; MALVA SYLVESTRIS LEAF; NIACINAMIDE; AVENA SATIVA LEAF; POPULUS TREMULOIDES LEAF; POPULUS ALBA LEAF; COCHLEARIA OFFICINALIS LEAF; SARSAPARILLA; NASTURTIUM OFFICINALE; VINCETOXICUM ATRATUM ROOT; PIMPINELLA SAXIFRAGA ROOT; (C10-C30)ALKYL METHACRYLATE ESTER; AMINOMETHYL PROPANEDIOL; SODIUM CITRATE; GLYCERIN

Metaderm Psoriasis Body and Scalp Spray

Active Ingredient

Achillea millefolium (3X H.P.U.S.*, 0.04%)
Aesculus hippocastanum (3X H.P.U.S.*, 0.04%)
Berberis vulgaris (3X H.P.U.S.*, 0.09%)
Conium maculatum (3X H.P.U.S.*, 0.21%)
Matricaria chamomilla (3X H.P.U.S.*, 0.05%)
Phytolacca decandra (3X H.P.U.S.*, 0.11%)
Rhus toxicodendron (3X H.P.U.S.*, 0.13%)
Sanguinaria canadensis (3X H.P.U.S.*, 0.08%)

Purpose

Cracking, Dryness, Rash, Scaling
Inflammation, itching
Burning, Itching, Redness, Scaling
Burning, Itching, Inflammation
Redness, Itching
Inflammation, Itching, Redness
Bleeding, Redness
Dryness, Irritation, Itching

*The letters H.P.U.S. indicate that the components in this product are officially monographed in the Homeopathic Pharmacopoeia of the United States.

Uses:

Fights recurrence of flaking, scaling, itching, redness, and skin
irritation associated with psoriasis

Warnings:

for external use only

Consult your doctor before using this product if the condition covers a
large area of the body

When using this product:

- Avoid contact with eyes.

Stop use and ask a doctor if:

condition worsens or does not improve after
regular use as directed.

Keep out of reach of children.

If swallowed, get medical help or
contact a Poison Control Center immediately. Test for allergy by
rubbing a small amount on skin first. Do not use if allergic to or
hypersensitive to any ingredient.

Directions:

For scalp, part hair, hold targeted nozzle no more than 1 inch from scalp, and spray at the roots to cover the affected area. For body, hold nozzle about 6 inches from skin and spray to cover the affected area. Lightly massage into scalp or skin with fingertips, No rinsing. Repeat on all affected areas and style hair as usual. Apply liberally to dry or wet skin 2 times daily.

Other ingredients:

Purified Water, Glycerin, Niacinamide, Phenoxyethanol,

1,2-Hexanediol, Caprylyl Glycol, Acrylates-C10-30 Alkyl

Acrylate Crosspolymer, Aminomethyl Propanol, Sodium Citrate,

Polysorbate-20, Citric Acid, Hamamelis virginiana, Hydrastis canadensis,

Avena sativa, Populus alba, Populus tremuloides, Cochlearia ocinalis,

Ervum lens, Scrophularia nodosa, Veronica ocinalis, Althaea ocinalis,

Sambucus nigra, Malva sylvestris, Nasturtium ocinale, Smilax medica,

Tussilago farfara, Pimpinella saxifraga, Vincetoxicum ocinale.